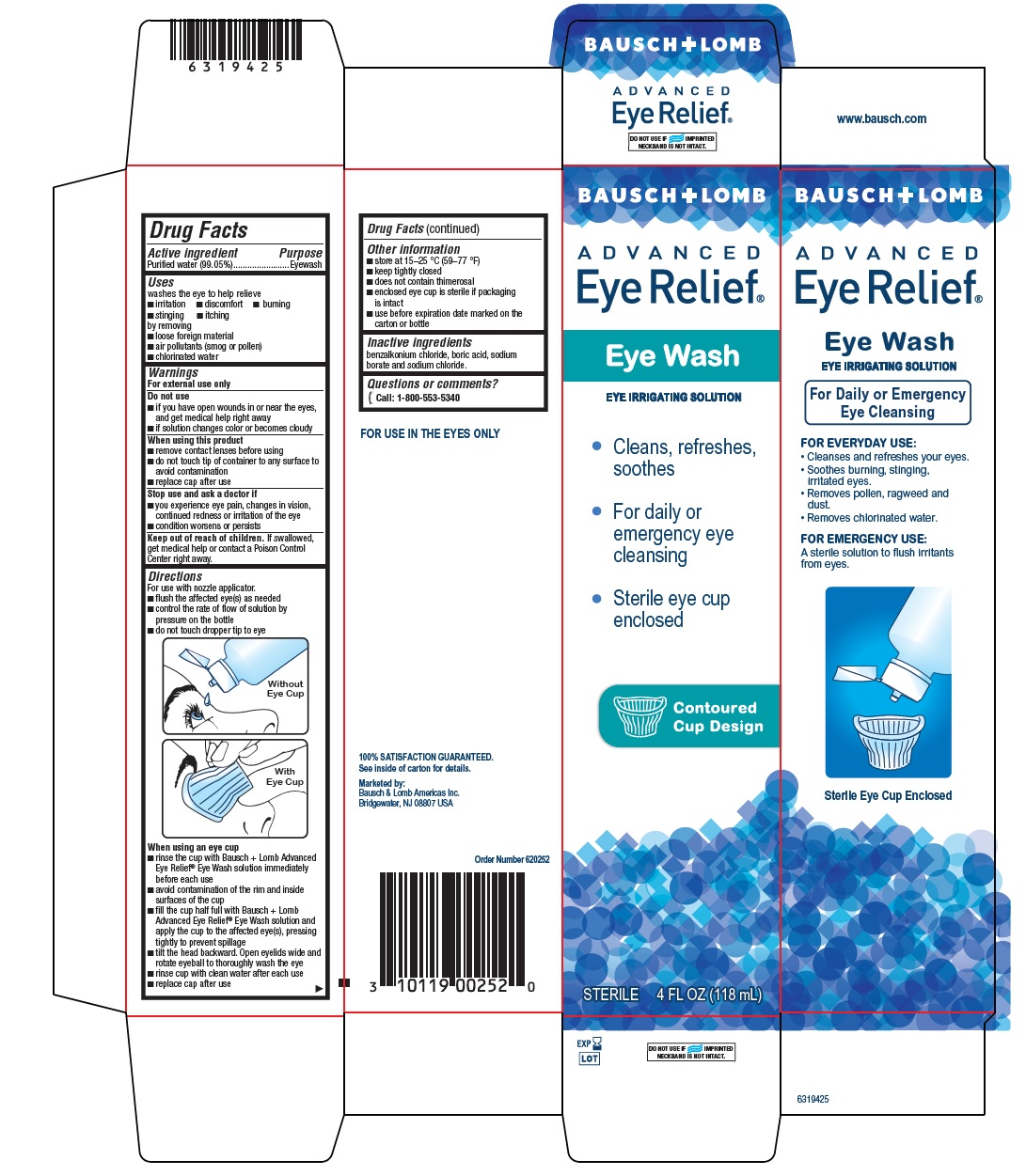 DRUG LABEL: Advanced Eye Relief Eye Wash
NDC: 24208-005 | Form: SOLUTION/ DROPS
Manufacturer: Bausch & Lomb Incorporated
Category: otc | Type: HUMAN OTC DRUG LABEL
Date: 20250217

ACTIVE INGREDIENTS: WATER 99.05 mL/100 mL
INACTIVE INGREDIENTS: BORIC ACID; SODIUM BORATE; SODIUM CHLORIDE; BENZALKONIUM

Drug Facts

Active ingredient

Purified water (99.05%)

Purpose

Eyewash

Uses

washes the eye to help relieve

- irritation
- stinging
- discomfort
- itching
- burning

by removing

- loose foreign material
- air pollutants (smog or pollen)
- chlorinated water

Warnings

For external use only

Do not use

- if you have open wounds in or near the eyes, and get medical help right away
- if solution changes color or becomes cloudy

When using this product

- remove contact lenses before using
- do not touch tip of container to any surface to avoid contamination
- replace cap after use

Stop use and ask a doctor if

- you experience eye pain, changes in vision, continued redness or irritation of the eye
- condition worsens or persists

Keep out of reach of children.

If swallowed, get medical help or contact a Poison Control Center right away.

Directions

For use with nozzle applicator.

- flush the affected eye(s) as needed
- control the rate of flow of solution by pressure on the bottle
- do not touch dropper tip to eye

[image eye] Without Eye Cup
[image eye] With Eye Cup

When using an eye cup

- rinse the cup with Bausch + Lomb Advanced Eye Relief®Eye Wash solution immediately before each use
- avoid contamination of the rim and inside surfaces of the cup
- fill the cup half full with Bausch + Lomb Advanced Eye Relief®Eye Wash solution and apply the cup to the affected eye(s), pressing tightly to prevent spillage
- tilt the head backward. Open eyelids wide and rotate eyeball to thoroughly wash the eye
- rinse cup with clean water after each use
- replace cap after use

Other information

- store at 15–25°C (59–77 °F)
- keep tightly closed
- does not contain thimerosal
- enclosed eye cup is sterile if packaging is intact
- use before expiration date marked on the carton or bottle

Inactive ingredients

benzalkonium chloride, boric acid, sodium borate and sodium chloride.

Questions or comments?

[phone icon] Call: 1-800-553-5340

FOR USE IN THE EYES ONLY

Marketed by:

Bausch & Lomb Americas Inc.

Bridgewater, NJ 08807 USA

Package/Label Principal Display Panel-Carton

BAUSCH + LOMB
ADVANCED
Eye Relief®

Eye Wash

EYE IRRIGATING SOLUTION

- Cleans, refreshes,
  soothes
- For daily or
  emergency eye
  cleansing
- Sterile eye cup
  enclosed

[image cup] Contoured
Cup Design

- STERILE 4 FL OZ (118 mL)
- 6319425